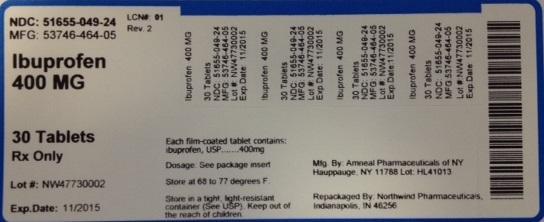 DRUG LABEL: Ibuprofen
NDC: 51655-049 | Form: TABLET, FILM COATED
Manufacturer: Northwind Pharmaceuticals
Category: prescription | Type: HUMAN PRESCRIPTION DRUG LABEL
Date: 20140520

ACTIVE INGREDIENTS: IBUPROFEN 400 mg/30 1

PACKAGE LABEL

NDC: 51655-049-24

MFG: 53746-464-05

Ibuprofen 400 MG

30 Tablets

Rx Only

Lot# NW47730002

Exp. Date: 11/2015

Each film coated tablet contains: ibuprofen, USP....400 mg

Dosage: See package insert

Store at 68 to 77 degrees F.

Store in a tight, light-resistant container (See USP).

Keep out of the reach of children.

Mfg by: Amneal Pharmaceuticals of NY Hauppage, NY 11788 Lot: HL41013

Repackaged by Northwind Pharmaceuticals, Indianapolis, IN 46256